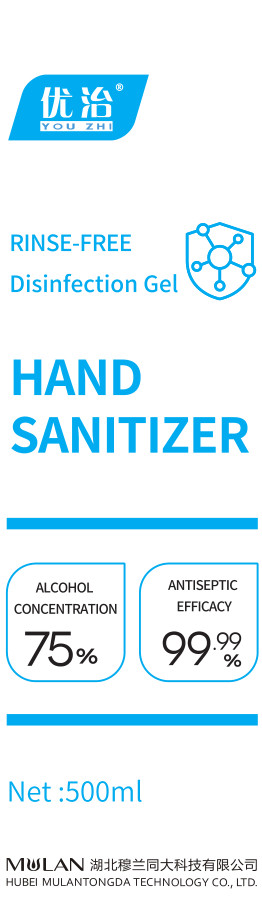 DRUG LABEL: YOUZHI  Hand  Sanitizer
NDC: 53023-001 | Form: GEL
Manufacturer: Hubei Mulan Tongda Technology Co., Ltd
Category: otc | Type: HUMAN OTC DRUG LABEL
Date: 20200414

ACTIVE INGREDIENTS: ALCOHOL 375 mL/500 mL
INACTIVE INGREDIENTS: CARBOMER HOMOPOLYMER, UNSPECIFIED TYPE; CUPRIC BIS(TRIETHANOLAMINE); WATER

DOSAGE AND ADMINISTRATION

Keep it sealed and store it in a cool, dry,well-ventilated environment away from light.

INACTIVE INGREDIENT

CARBOMER 940

TRIETHANOLAMINE

PURIFIED WATER

INDICATIONS AND USAGE

1.Hand Antisepsis: Apply the gel evenly on hand 1-2 times and allow action for one minute whereas surgical hand disinfection entails respective two times and 3 minutes.
2.2.Skin Antisepsis:Apply the gel evenly on the skin 2 times and allow action for 3 minutes.

ACTIVE INGREDIENT

Ethanol

PURPOSE

Disinfection
Sterilization
No Rinseing

keep out of children

WARNINGS

1.The disinfectant is for external use only! Keep out of the reach of the children!
2.It's flammable. Keep it away from flames.
3.Individuals allergic to alcohol should use the product cautiously.
4.Keep it sealed and store it in a cool, dry,well-ventilated environment away from light.
5.Inappropriate for disinfecting the surface of the lipid-soluble object.